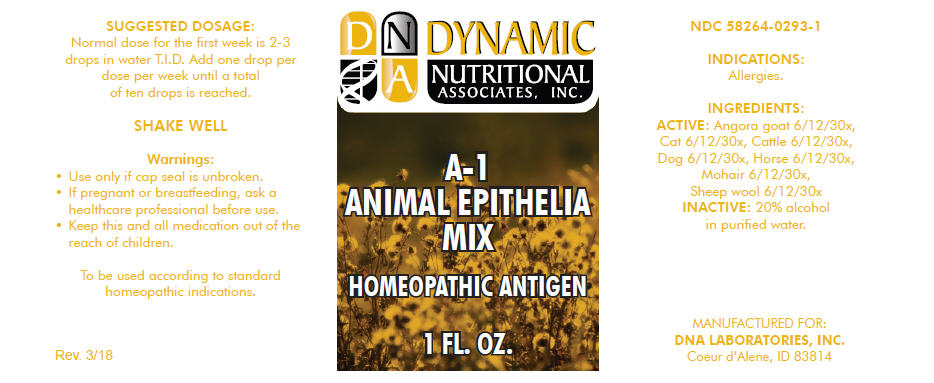 DRUG LABEL: A-1
NDC: 58264-0293 | Form: SOLUTION
Manufacturer: DNA Labs, Inc.
Category: homeopathic | Type: HUMAN OTC DRUG LABEL
Date: 20250109

ACTIVE INGREDIENTS: CAPRA HIRCUS SKIN 30 [hp_X]/1 mL; FELIS CATUS SKIN 30 [hp_X]/1 mL; BOS TAURUS SKIN 30 [hp_X]/1 mL; CANIS LUPUS FAMILIARIS SKIN 30 [hp_X]/1 mL; EQUUS CABALLUS SKIN 30 [hp_X]/1 mL; CAPRA HIRCUS HAIR 30 [hp_X]/1 mL; SHEEP WOOL 30 [hp_X]/1 mL
INACTIVE INGREDIENTS: ALCOHOL; WATER

A-1

NDC 58264-0293-1

INDICATIONS

PURPOSE

Allergies.

INGREDIENTS

ACTIVE

Angora goat 6/12/30x, Cat 6/12/30x, Cattle 6/12/30x, Dog 6/12/30x, Horse 6/12/30x, Mohair 6/12/30x, Sheep wool 6/12/30x

INACTIVE

20% alcohol in purified water.

SUGGESTED DOSAGE

Normal dose for the first week is 2-3 drops in water T.I.D. Add one drop per dose per week until a total of ten drops is reached.

STORAGE AND HANDLING

SHAKE WELL

Warnings

- Use only if cap seal is unbroken.

PREGNANCY OR BREAST FEEDING

- If pregnant or breastfeeding, ask a healthcare professional before use.

KEEP OUT OF REACH OF CHILDREN

- Keep this and all medication out of the reach of children.

To be used according to standard homeopathic indications.

PRINCIPAL DISPLAY PANEL - 1 FL. OZ. Bottle Label

DYNAMIC
NUTRITIONAL
ASSOCIATES, INC.

A-1
ANIMAL EPITHELIA
MIX

HOMEOPATHIC ANTIGEN

1 FL. OZ.